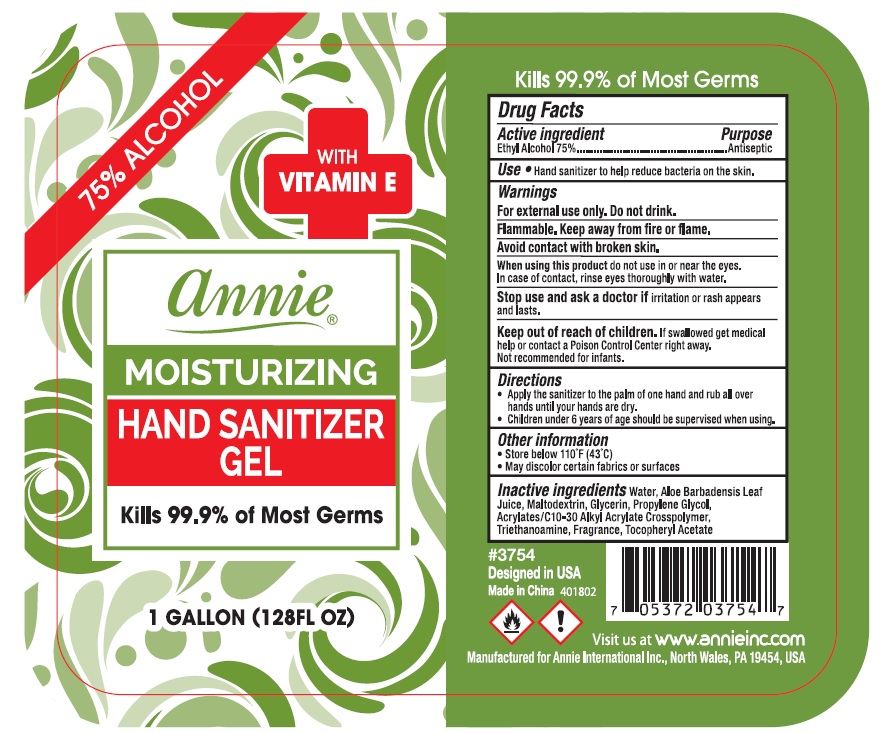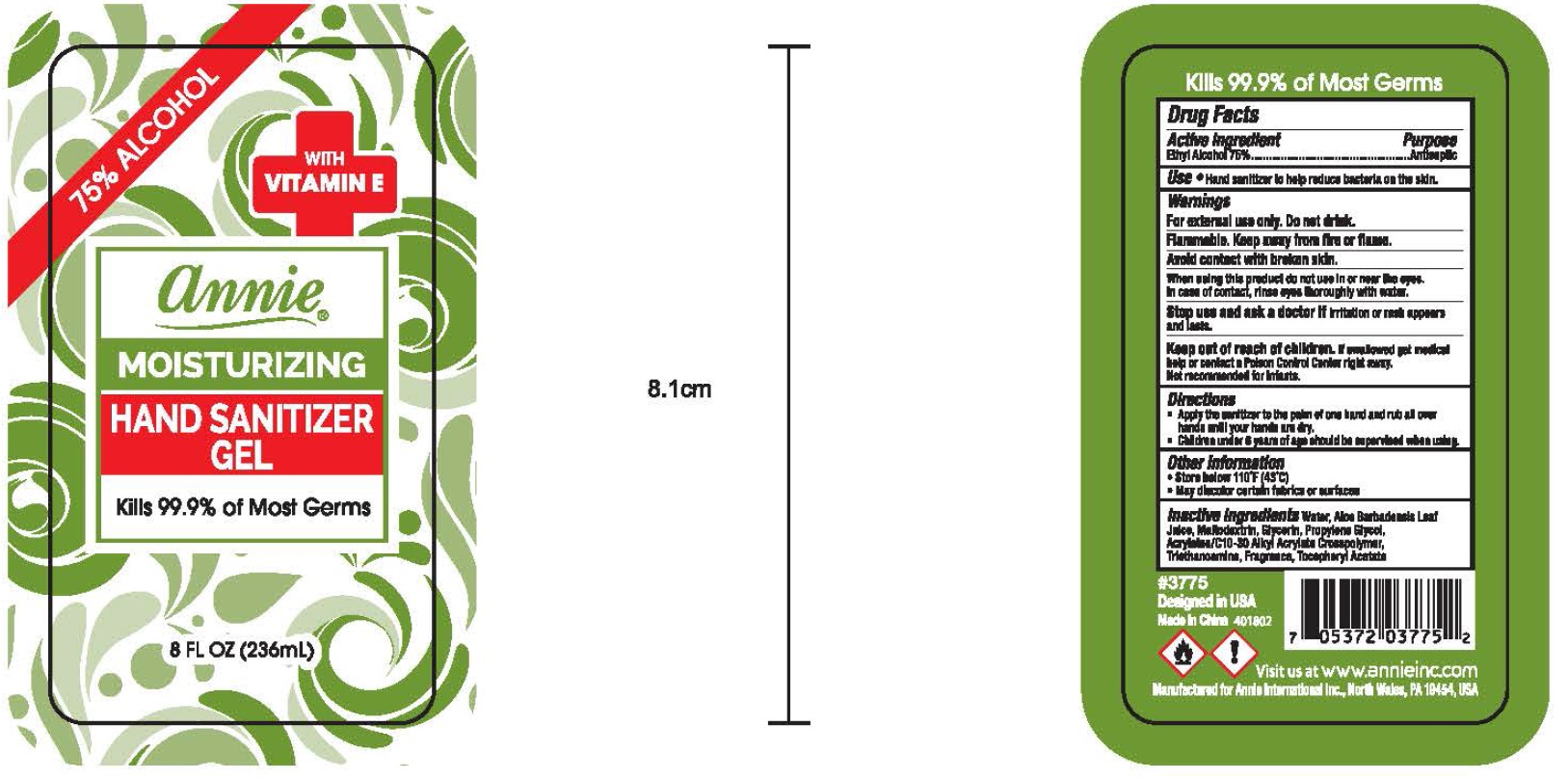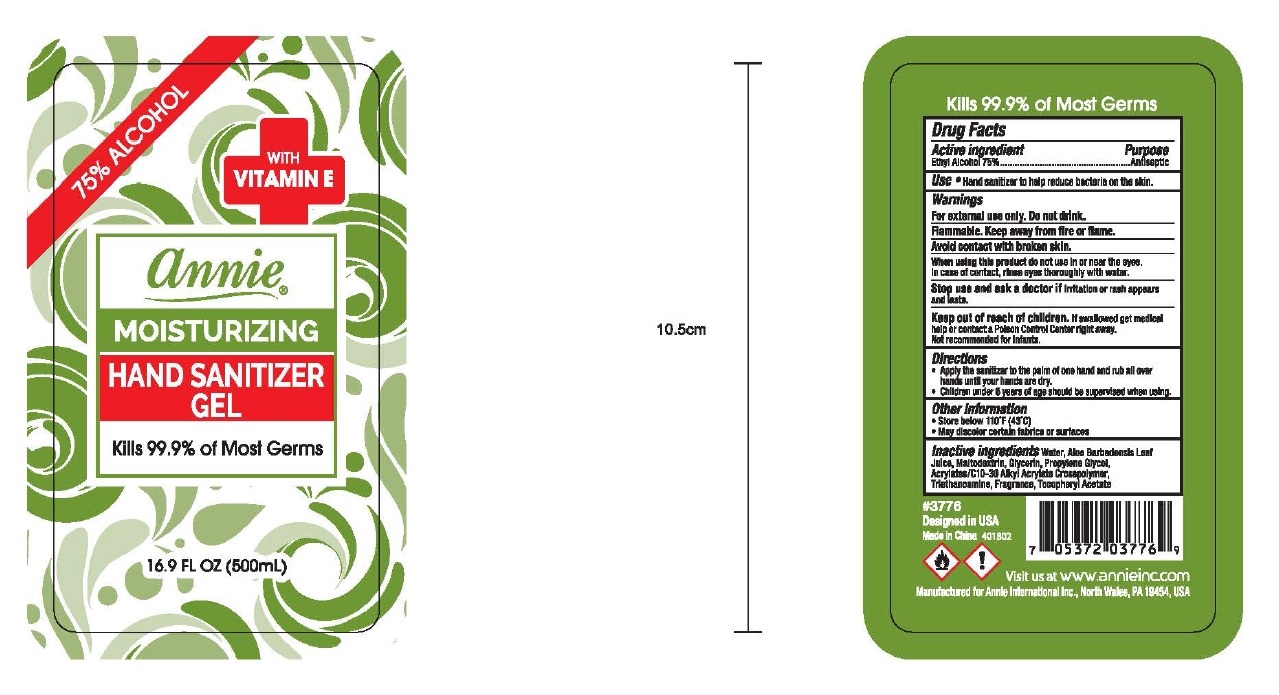 DRUG LABEL: Annie
NDC: 75629-750 | Form: GEL
Manufacturer: ANNIE INTERNATIONAL, INC
Category: otc | Type: HUMAN OTC DRUG LABEL
Date: 20200713

ACTIVE INGREDIENTS: ALCOHOL 70 mL/100 mL
INACTIVE INGREDIENTS: WATER; ALOE VERA LEAF; MALTODEXTRIN; GLYCERIN; PROPYLENE GLYCOL; CARBOMER INTERPOLYMER TYPE A (ALLYL SUCROSE CROSSLINKED); TROLAMINE; .ALPHA.-TOCOPHEROL ACETATE

Active Ingredient

Ethyl Alcohol 75%

Purpose

Antiseptic

Use

Hand Sanitizer to help reduce bacteria on the skin

Warnings

For external use only. Do not drink.

Flammable. Keep away from fire or flame

Avoid contact with broken skin

When using this product

do not use in or near the eyes. In case of contact, rinse eyes thoroughly with water.

Stop use and ask a doctor if

irritation or rash appears and lasts

Keep out of reach of children.

If swallowed, get medical help or contact a Poison Control Center right away.

Not recommended for infants

Directions

- Apply the sanitizer to the palm of one hand and rub all over hands until your hands are dry
- Children under 6 years of age should be supervised when using

Other information

- Store below 110°F (43°C)
- May discolor certain fabrics or surfaces

Inactive ingredients

Water (Aqua), Aloe Barbadensis Leaf Juice, Maltodextrin, Glycerin, Propylene Glycol, Acrylates/C10-30 Alkyl Acrylate Crosspolymer, Triethanolamine, Fragrance, Tocopheryl Acetate.

Principal Display Panel

NDC 75629-750-08

annie®

MOISTURIZING HAND SANITIZER GEL WITH VITAMIN E

75% Alcohol

Kills 99.9% of Most Germs

8 FL OZ (236mL)

NDC 75629-750-17

annie®

MOISTURIZING HAND SANITIZER GEL WITH VITAMIN E

75% Alcohol

Kills 99.9% of Most Germs

16.9 FL OZ (500mL)

NDC 75629-750-01

annie®

MOISTURIZING HAND SANITIZER GEL WITH VITAMIN E

75% Alcohol

Kills 99.9% of Most Germs

1 GALLON (128 FL OZ)